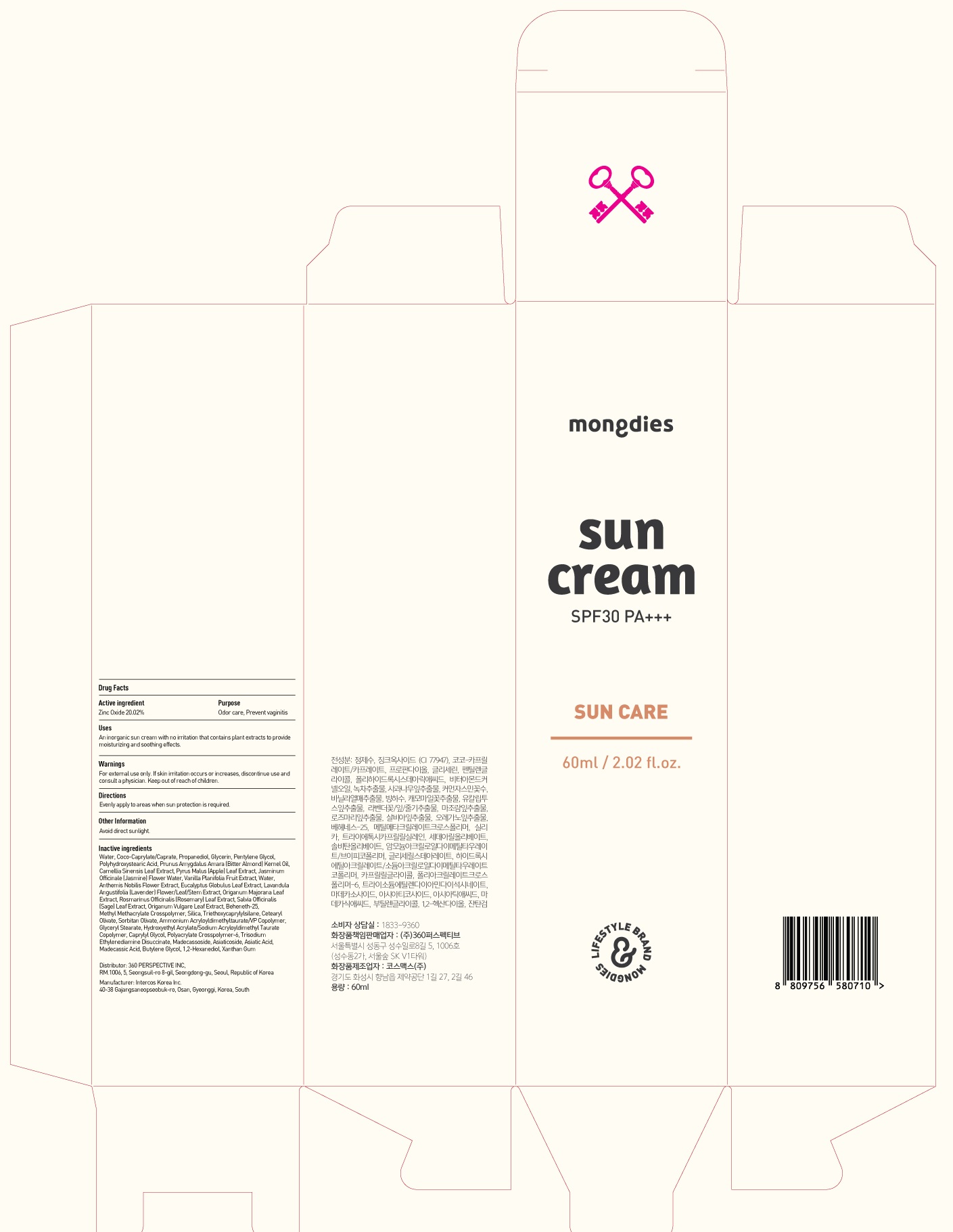 DRUG LABEL: Mongdies excellent sun
NDC: 70477-030 | Form: CREAM
Manufacturer: 360Perspective Inc.
Category: otc | Type: HUMAN OTC DRUG LABEL
Date: 20210910

ACTIVE INGREDIENTS: Zinc Oxide 12.01 g/60 mL
INACTIVE INGREDIENTS: Water; Glycerin; Pentylene Glycol

ACTIVE INGREDIENT

Zinc Oxide 20.02%

PURPOSE

Sunscreen

WARNINGS

For external use only. If skin irritation occurs or increases, discontinue use and consult a physician. Keep out of reach of children.

KEEP OUT OF REACH OF CHILDREN

Uses

An inorganic sun cream with no irritation that contains plant extracts to provide moisturizing and soothing effects.

Directions

Evenly apply to areas when sun protection is required.

Other Information

Avoid direct sunlight.

INACTIVE INGREDIENTS

Water, Coco-Caprylate/Caprate, Propanediol, Glycerin, Pentylene Glycol, Polyhydroxystearic Acid, Prunus Amygdalus Amara (Bitter Almond) Kernel Oil, Camellia Sinensis Leaf Extract, Pyrus Malus (Apple) Leaf Extract, Jasminum Officinale (Jasmine) Flower Water, Vanilla Planifolia Fruit Extract, Water, Anthemis Nobilis Flower Extract, Eucalyptus Globulus Leaf Extract, Lavandula Angustifolia (Lavender) Flower/Leaf/Stem Extract, Origanum Majorana Leaf Extract, Rosmarinus Officinalis (Rosemary) Leaf Extract, Salvia Officinalis (Sage) Leaf Extract, Origanum Vulgare Leaf Extract, Beheneth-25, Methyl Methacrylate Crosspolymer, Silica, Triethoxycaprylylsilane, Cetearyl Olivate, Sorbitan Olivate, Ammonium Acryloyldimethyltaurate/VP Copolymer, Glyceryl Stearate, Hydroxyethyl Acrylate/Sodium Acryloyldimethyl Taurate Copolymer, Caprylyl Glycol, Polyacrylate Crosspolymer-6, Trisodium Ethylenediamine Disuccinate, Madecassoside, Asiaticoside, Asiatic Acid, Madecassic Acid, Butylene Glycol, 1,2-Hexanediol, Xanthan Gum